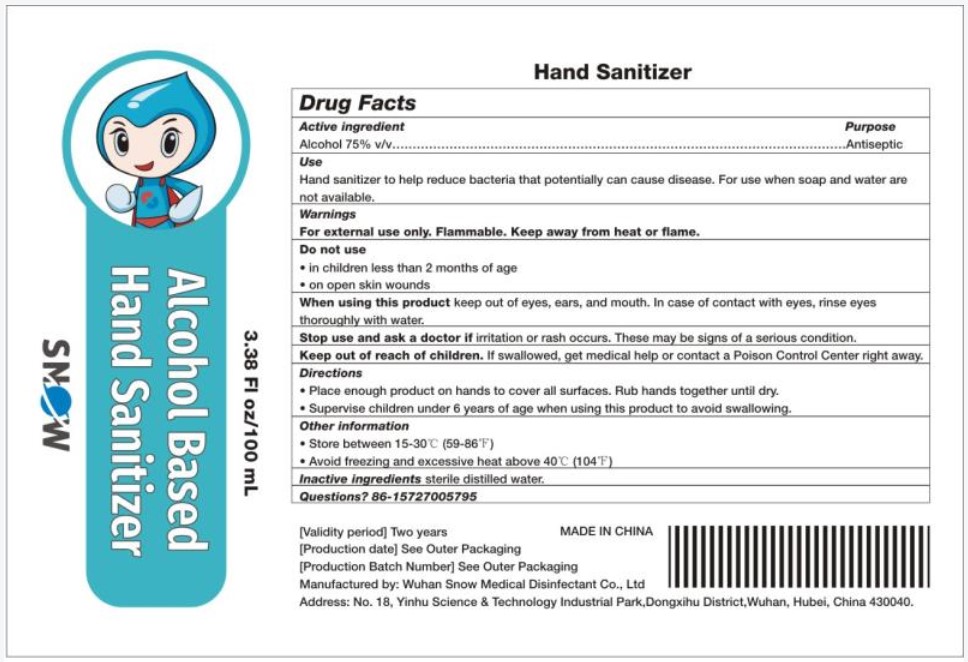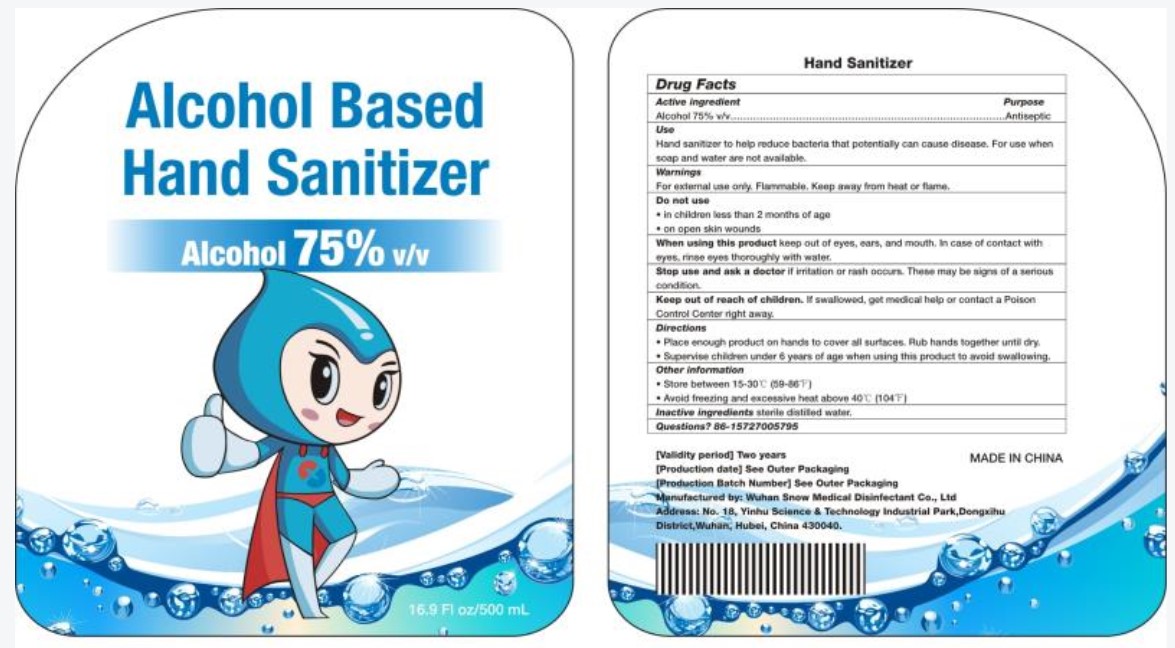 DRUG LABEL: ALCOHOL BASED HAND SANITIZER
NDC: 80334-0831 | Form: SOLUTION
Manufacturer: Wuhan Snow Medical Disinfectant Co., Ltd
Category: otc | Type: HUMAN OTC DRUG LABEL
Date: 20231227

ACTIVE INGREDIENTS: ALCOHOL 75 mL/100 mL
INACTIVE INGREDIENTS: WATER

Active Ingredient(s)

Alcohol 75% v/v. Purpose: Antiseptic

Purpose

Antiseptic, Hand Sanitizer

Use

Hand Sanitizer to help reduce bacteria that potentially can cause disease. For use when soap and water are not available.

Warnings

For external use only. Flammable. Keep away from heat or flame

Do not use

- in children less than 2 months of age
- on open skin wounds

When using this product keep out of eyes, ears, and mouth. In case of contact with eyes, rinse eyes thoroughly with water.
Stop use and ask a doctor if irritation or rash occurs. These may be signs of a serious condition.
Keep out of reach of children. If swallowed, get medical help or contact a Poison Control Center right away.

Stop use and ask a doctor if irritation or rash occurs. These may be signs of a serious condition.

Keep out of reach of children. If swallowed, get medical help or contact a Poison Control Center right away.

Directions

- Place enough product on hands to cover all surfaces. Rub hands together until dry.
- Supervise children under 6 years of age when using this product to avoid swallowing.

Other information

- Store between 15-30C (59-86F)
- Avoid freezing and excessive heat above 40C (104F)

Inactive ingredients

sterile distilled water

Package Label - Principal Display Panel

100 mL NDC: 80334-0831-1

Package Label - Principal Display Panel

500 mL NDC: 80334-0831-2